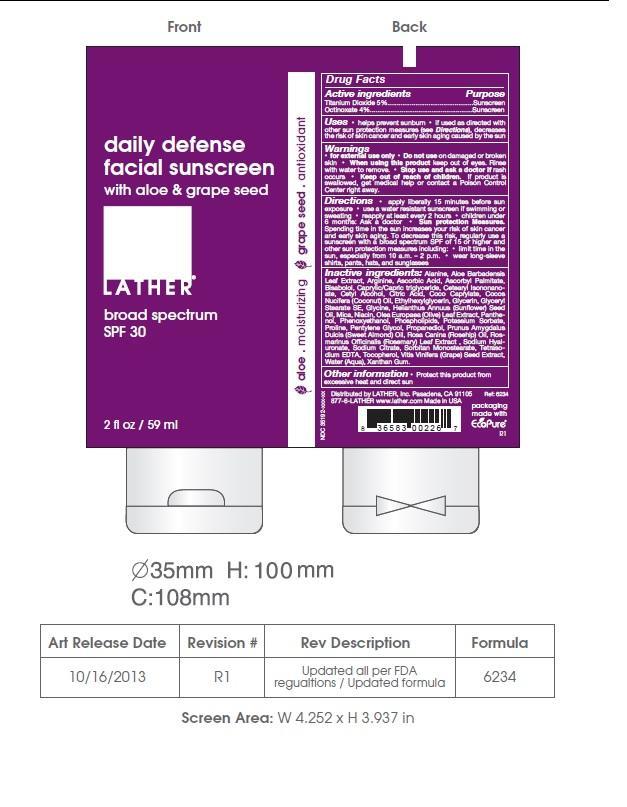 DRUG LABEL: Shimmery Sun
NDC: 35192-014 | Form: LOTION
Manufacturer: CA-BOTANA INTERNATIONAL
Category: otc | Type: HUMAN OTC DRUG LABEL
Date: 20131010

ACTIVE INGREDIENTS: OCTINOXATE 2 g/113.4 g; TITANIUM DIOXIDE 2.5 g/113.4 g
INACTIVE INGREDIENTS: ALANINE; ALOE VERA LEAF; ARGININE; ASCORBIC ACID; ASCORBYL PALMITATE; .ALPHA.-BISABOLOL, (+/-)-; CAPRYLIC/CAPRIC MONO/DIGLYCERIDES; CETEARYL ISONONANOATE; CETYL ALCOHOL; CITRIC ACID MONOHYDRATE; COCONUT; ETHYLHEXYLGLYCERIN; GLYCERIN; GLYCERYL MONOSTEARATE; GLYCINE; SUNFLOWER OIL; MICA; NIACIN; OLEA EUROPAEA LEAF; PANTHENOL; PHENOXYETHANOL; LECITHIN, SOYBEAN; POTASSIUM SORBATE; SODIUM PYROPHOSPHATE; PENTYLENE GLYCOL; PROPANEDIOL; ALMOND OIL; ROSA MOSCHATA OIL; ROSEMARY; HYALURONATE SODIUM; SODIUM CITRATE; SORBITAN; TOCOPHEROL; GRAPE SEED OIL; XANTHAN GUM; WATER

Sunscreen Shimmery Sun

WARNINGS

For external use only. Do not use on damaged or broken skin. When using this product keep out of eyes. Rinse with water to remove. Stop use and ask a doctor if rash occurs. Keep out of reach of children. If product is swallowed, get medical help or contact a poison control center right away.

DOSAGE AND ADMINISTRATION

Helps prevent sunburn. If used as directed with other sun protection measured decreases the risk of skin cancer and early skin aging caused by the sun. Apply liberally 15 minutes before sun exposure. Use a water resistant sunscreen if swimming or sweating. Reapply: at least 2 hours. Children under 6 months: Ask a doctor. Sun protection measurements. Spending time in the sun increases your risk of skin cancer and early skin aging. To decrease this risk, regularly use a sunscreen with a broad spectrum SPF of 15 or higher and other sun protection measures including: limit time in the sun, especially from 10 a.m - 2 p.m. Wear long-sleeve shirts, pants, hats, and sunglasses. Protect this product from excessive heat and direct sun

INACTIVE INGREDIENT

ALANINE, ALOE VERA LEAF, ARGININE, ASCORBIC ACID, ASCORBYL PALMITATE, .ALPHA.-BISABOLOL, (+/-)-,CAPRYLIC/CAPRIC MONO/DIGLYCERIDES, CETEARYL ISONONANOATE, CETYL ALCOHOL, CITRIC ACID MONOHYDRATE, COCONUT, ETHYLHEXYLGLYCERIN, GLYCERIN, GLYCERYL MONOSTEARATE, GLYCINE, SUNFLOWER OIL, MICA, NIACIN, OLEA EUROPAEA LEAF, PANTHENOL, PHENOXYETHANOL, LECITHIN, SOYBEAN, POTASSIUM SORBATE, SODIUM PYROPHOSPHATE, PENTYLENE GLYCOL, PROPANEDIOL, ALMOND OIL, ROSA MOSCHATA OIL, ROSEMARY, HYALURONATE SODIUM, SODIUM CITRATE, SORBITAN, TOCOPHEROL, UREA, GRAPE SEED OIL, XANTHAN GUM, WATER

PURPOSE

Sunscreen

KEEP OUT OF REACH OF CHILDREN

For external use only.
Avoid contact with eyes.
Keep out of reach of children.
Do not apply to open wounds.
STOP USE AND ask a doctor if condition worsens or
symptoms persist for more than seven days, discontinue
use of the product.

ACTIVE INGREDIENT

Titanium Dioxide, Octinoxate